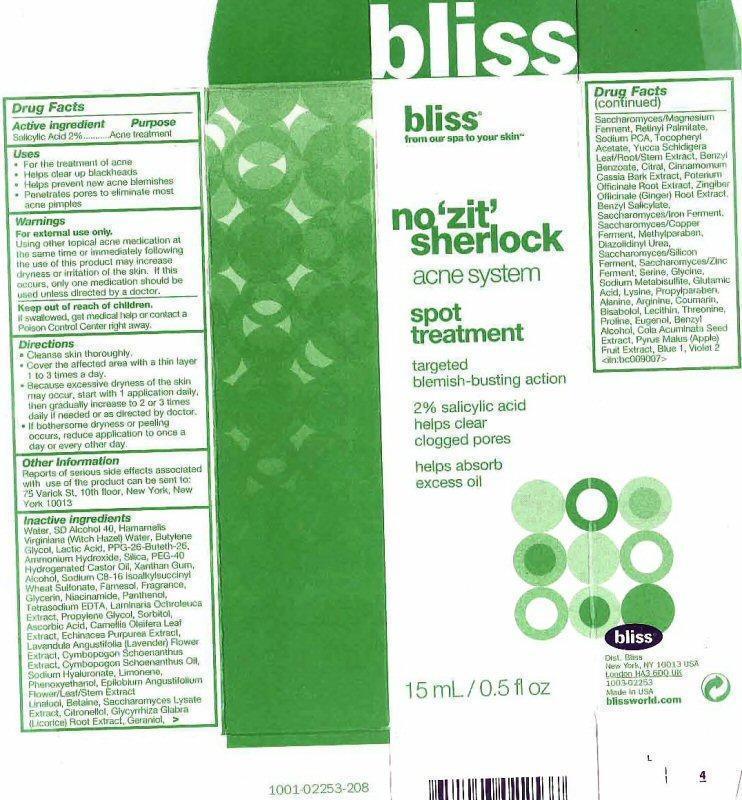 DRUG LABEL: no zit sherlock acnespot treatment
  
NDC: 67038-104 | Form: GEL
Manufacturer: Bliss World LLC
Category: otc | Type: HUMAN OTC DRUG LABEL
Date: 20120611

ACTIVE INGREDIENTS: SALICYLIC ACID 3 mg/15 mL
INACTIVE INGREDIENTS: WATER; ALCOHOL; HAMAMELIS VIRGINIANA TOP WATER; BUTYLENE GLYCOL; LACTIC ACID; PPG-26-BUTETH-26; AMMONIA; SILICON DIOXIDE; POLYOXYL 40 HYDROGENATED CASTOR OIL; XANTHAN GUM; FARNESOL; GLYCERIN; NIACINAMIDE; PANTHENOL; EDETATE SODIUM; LAMINARIA OCHROLEUCA; PROPYLENE GLYCOL; SORBITOL; ASCORBIC ACID; CAMELLIA OLEIFERA LEAF; ECHINACEA PURPUREA; LAVANDULA ANGUSTIFOLIA FLOWER; CYMBOPOGON SCHOENANTHUS TOP; CYMBOPOGON SCHOENANTHUS OIL; HYALURONATE SODIUM; LIMONENE, (+)-; PHENOXYETHANOL; EPILOBIUM ANGUSTIFOLIUM FLOWERING TOP; LINALOOL, (+/-)-; BETAINE; SACCHAROMYCES LYSATE; .BETA.-CITRONELLOL, (R)-; GLYCYRRHIZA GLABRA; GERANIOL; VITAMIN A PALMITATE; SODIUM PYRROLIDONE CARBOXYLATE; .ALPHA.-TOCOPHEROL ACETATE; YUCCA SCHIDIGERA; BENZYL BENZOATE; CITRAL; CHINESE CINNAMON; SANGUISORBA OFFICINALIS ROOT; GINGER; BENZYL SALICYLATE; METHYLPARABEN; DIAZOLIDINYL UREA; SERINE; GLYCINE; SODIUM METABISULFITE; GLUTAMIC ACID; LYSINE; PROPYLPARABEN; ALANINE; ARGININE; COUMARIN; LEVOMENOL; LECITHIN, SOYBEAN; THREONINE; PROLINE; EUGENOL; BENZYL ALCOHOL; COLA ACUMINATA SEED; APPLE; FD&C BLUE NO. 1; D&C VIOLET NO. 2

Active ingredient

Drug Facts

Active ingredient

Salicylic acid 2%

Purpose

Acne treatment

Keep out of reach of children. If swallowed, get medical help or contact a Poison Control Center right away.

Uses

- For the treatment of acne
- Helps clear up blackheads
- Helps prevent new acne blemishes
- Penetrates pores to eliminate most acne pimples

Warnings

For external use only.

Using other topical acne medication at the same time or immediately following the use of this product may increase dryness or irritation of the skin. It this occurs, only one medication should be used unless directed by a doctor.

Directions

Enter section text here

Other Information

Enter section text here

Inactive ingredients

Water, SD Alcohol 40, Hamamelis Virginiana (Witch Hazel) Water, Butylene Glycol, Lactic Acid, PPG-26-Buteth-26, Ammonium Hydroxide, Silica, PEG-40 Hydrogenated Castor Oil, Xanthan Gum, Alcohol, Sodium C8-16 Isoalkylsuccinyl Wheat Sulfonate, Farnesol, Fragrance, Glycerin, Niacinamide, Panthenol, Tetrasodium EDTA, Laminaria Ochroleuca Extract, Propylene Glycol, Sorbitol, Ascorbic Acid, Camellia Oleifera Leaf Extract, Echinacea Purpurea Extract, Lavandula Angustifolia (Lavender) Flower Extract, Cymbopogon Schoenanthus Extract, Cymbopogon Schoenanthus Oil, Sodium Hyaluronate, Limonene, Phenoxyethanol, Epilobium Angustifolium Flower/Leaf/Stem Extract, Linalool, Betaine, Saccharomyces Lysate Extract, Citronellol, Glycyrrhiza Glabra (Licorice) Root Extract, Geraniol, Saccharomyces/Magnesium Ferment, Retinyl Palmitate, Sodium PCA, Tocopherly Acetate, Yucca Schidigera Leaf/Root/Stem Extract, Benzyl Benzoate, Citral, Cinnamomum Cassia Bark Extract, Poterium Officinale Root Extract, Zingiber Officinale (Ginger) Root Extract, Benzyl Salicylate, Saccharomyces/Iron Ferment, Saccharomyces/Copper Ferment, Methylparaben, Diazolidinyl Urea, Saccharomyces/Silicon Ferment, Saccharomyces/Zinc Ferment Serine, Glycine, Sodium Metabisulfite, Glutamic Acid, Lysine, Propylparaben, Alanine, Arginine, Coumarin, Bisabolol, Lecithin, Threonine, Proline, Eugenol, Benzyl Alcohol, Cola Acuminata Seed Extract, Pyrus Malus (Apple) Fruit Extract, Blue 1, Violet 2

Package Label

bliss from our spa to your skin

no 'zit' sherlock acne system spot treatment

targeted blemish-busting action 2% salicylic acid helps clear clogged pores helps absorb excess oil

15mL/ 0.5 fl oz

bliss Dist. Bliss New York, NY 10013 USA London HA3 600 UK 1003-02253 Made in USA blissworld.com